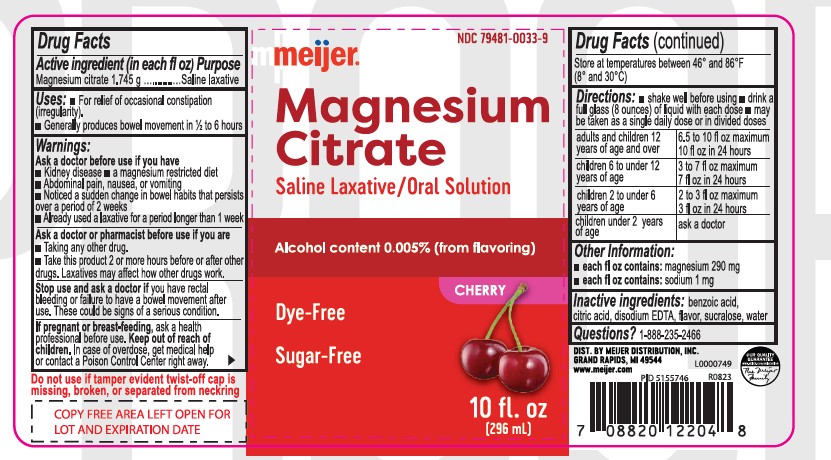 DRUG LABEL: Magnesium Citrate
NDC: 79481-0033 | Form: LIQUID
Manufacturer: Meijer Distribution Inc
Category: otc | Type: HUMAN OTC DRUG LABEL
Date: 20251216

ACTIVE INGREDIENTS: MAGNESIUM CITRATE 1.745 g/29.6 mL
INACTIVE INGREDIENTS: BENZOIC ACID; WATER; CITRIC ACID MONOHYDRATE; SUCRALOSE; EDETATE DISODIUM ANHYDROUS

Meijer Magnesium Citrate Oral Solution - Cherry

Active Ingredient

Magnesium citrate 1.745 g (in each fl oz)

Purpose

Saline laxative

Uses

- For relief of occasional constipation (irregularity)

- Generally produces bowel movement in 1/2 to 6 hours

Warnings

Ask a doctor before use if you have

- Kidney disease
- a magnesium restricted diet
- Abdominal pain, nausea, or vomiting
- Noticed a sudden change in bowel habits that persists over a period of 2 weeks
- Already used a laxative for a period longer than 1 week

Ask a doctor or pharmacisy before use if you are

- Taking any other drug.
- Take this product 2 or more hours before or after other drugs. Laxatives may affect how other drugs work.

Stop use and ask a doctor if

you have rectal bleeding or failure to have a bowel movement after use. These could be signs of a serious condition.

If pregnant or breast-feeding,

ask health professional before use.

Keep out of reach of children.

In case of overdose, get medical help or contact a Poison Control Center right away.

STORAGE AND HANDLING

Store at temperatures between 46° and 86°F (8° and 30° C)

Directions

- shake well before using
- drink a full glass (8 ounces) of liquid with each dose
- may be taken as a single daily dose or in divided doses
  adults and children 12 years of age and over | 6.5 to 10 fl oz maximum 10 fl oz in 24 hours
  children 6 to under 12 years of age | 3 to 7 fl oz maximum 7 fl oz in 24 hours
  children 2 to under 6 years of age | 2 to 3 fl oz in 24 hours maximum 3 fl oz in 24 hours
  children under 2 years of age | ask a doctor

Other Information

each fl oz contains: magnesium 290 mg
each fl oz contains: sodium 1 mg

Inactive Ingredients

benzoic acid, citric acid, disodium EDTA, flavor, sucralose, water

Questions?

1-888-235-2466

DIST. MEIJER DISTRIBUTION, INC.

GRAND RAPIDS, MI 49544

www.meijer.com L0000749

R0823

Do not use if tamper evident twist-off cap is

missing, broken, or separated from neckring

PACKAGE LABEL

NDC 79481-0033-9

meijer®

CHERRY FLAVOR

magnesium

citrate

Saline Laxative/ Oral Solution

• DYE-FREE • SUGAR-FREE

Alcohol content 0.005% (from flavouring)

10 FL OZ (296 mL)